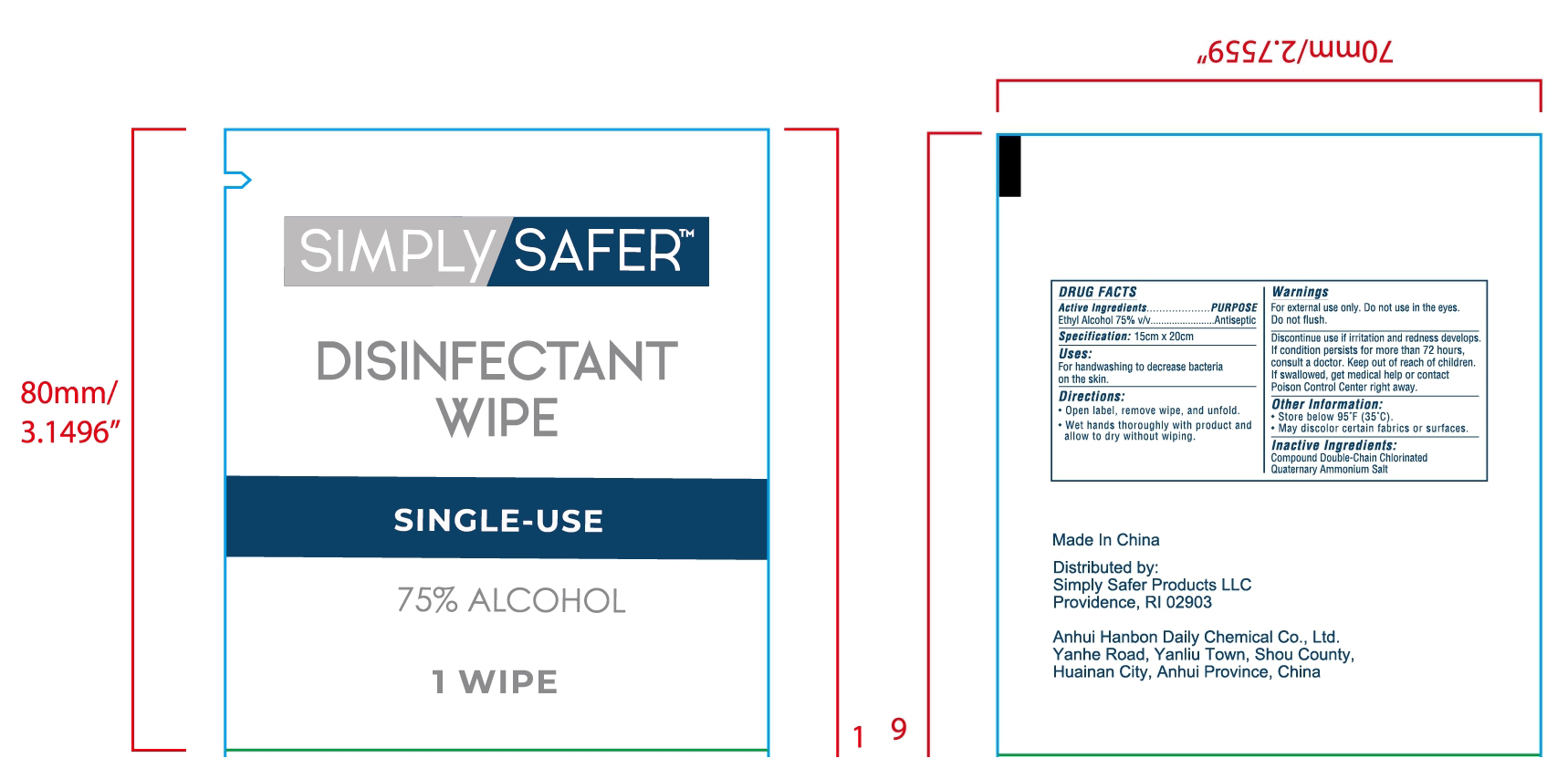 DRUG LABEL: Simply Safer Disinfectant Wipe
NDC: 79754-002 | Form: CLOTH
Manufacturer: Simply Safer Products Llc
Category: otc | Type: HUMAN OTC DRUG LABEL
Date: 20200730

ACTIVE INGREDIENTS: ALCOHOL 75 mL/100 g
INACTIVE INGREDIENTS: GLYCERIN; WATER; PHENOXYETHANOL; DIDECYLDIMONIUM CHLORIDE; BENZALKONIUM CHLORIDE; CETYLPYRIDINIUM CHLORIDE; N-ALKYL ETHYLBENZYL DIMETHYL AMMONIUM CHLORIDE (C12-C14)

DISINFECTANT WIPES

Active Ingredient(s)

Alcohol 75% Purpose: Antiseptic

Purpose

Antiseptic, wipes

Uses

For handwashing to decrease bacteria on the skin.

Directions

- Open label, remove wipe, and unfold
- Wet hands thoroughly with product and allow to dry without wiping

Warnings

For external use only. Do not use in the eyes. Do not flush.

STOP USE

Discontinue use if irritation and redness develops. If condition persists for more than 72 hours, consult a doctor.

Keep out of reach of children. If swallowed, get medical help or contact a Poison Control Center right away.

Other information

- Store below 95F (35C)
- May discolor certain fabrics or surfaces

Inactive ingredients

BENZALKONIUM CHLORIDE, WATER, CETYLPYRIDINIUM CHLORIDE, DIDECYLDIMONIUM CHLORIDE, PHENOXYETHANOL, GLYCERIN, N-ALKYL ETHYLBENZYL DIMETHYL AMMONIUM CHLORIDE (C12-C14)

Package Label - Principal Display Panel

1PC NDC: 79754-002-01